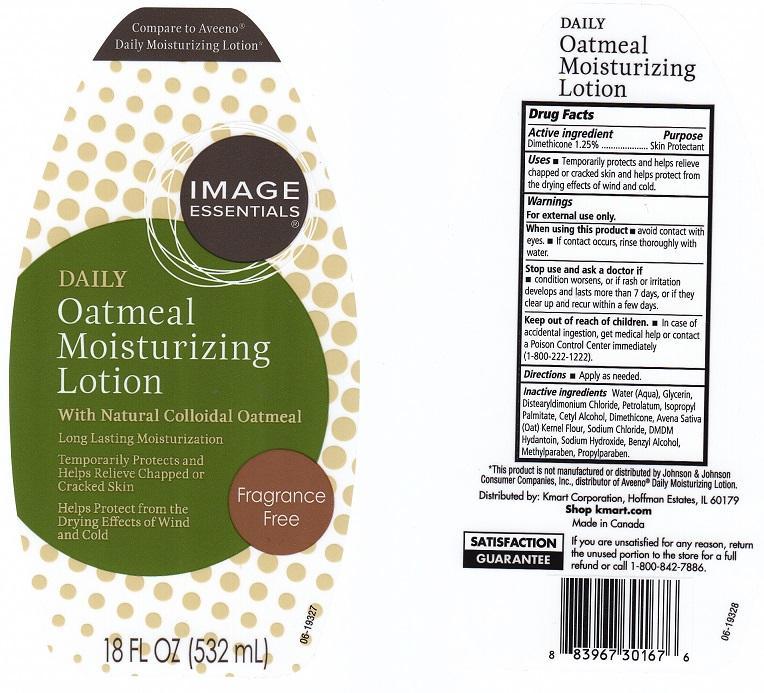 DRUG LABEL: IMAGE ESSENTIALS
NDC: 49738-320 | Form: LOTION
Manufacturer: KMART CORPORATION
Category: otc | Type: HUMAN OTC DRUG LABEL
Date: 20140226

ACTIVE INGREDIENTS: DIMETHICONE 12.5 mg/1 mL
INACTIVE INGREDIENTS: WATER; GLYCERIN; DISTEARYLDIMONIUM CHLORIDE; PETROLATUM; ISOPROPYL PALMITATE; CETYL ALCOHOL; OATMEAL; SODIUM CHLORIDE; DMDM HYDANTOIN; SODIUM HYDROXIDE; BENZYL ALCOHOL; METHYLPARABEN; PROPYLPARABEN

DRUG FACTS

ACTIVE INGREDIENT

DIMETHICONE 1.25%

PURPOSE

SKIN PROTECTANT

USES

TEMPORARILY PROTECTS AND HELPS RELIEVE CHAPPED OR CRACKED SKIN AND HELPS PROTECT FROM THE DRYING EFFECTS OF WIND AND COLD

WARNINGS

FOR EXTERNAL USE ONLY

WHEN USING THIS PRODUCT

AVOID CONTACT WITH EYES. IF CONTACT OCCURS, RINSE THOROUGHLY WITH WATER

STOP USE AND ASK A DOCTOR IF

CONDITION WORSENS, OR IF RASH OR IRRITATION DEVELOPS AND LASTS MORE THAN 7 DAYS, OR IF THEY CLEAR UP AND RECUR WITHIN A FEW DAYS

KEEP OUT OF REACH OF CHILDREN

IN CASE OF ACCIDENTAL INGESTION, GET MEDICAL HELP OR CONTACT A POISON CONTROL CENTER IMMEDIATELY (1-800-222-1222)

DIRECTIONS

APPLY AS NEEDED

INACTIVE INGREDIENTS

WATER (AQUA), GLYCERIN, DISTEARYLDIMONIUM CHLORIDE, PETROLATUM, ISOPROPYL PALMITATE, CETYL ALCOHOL, AVENA SATIVA (OAT) KERNEL FLOUR, SODIUM CHLORIDE, DMDM HYDANTOIN, SODIUM HYDROXIDE, BENZYL ALCOHOL, METHYLPARABEN, PROPYLPARABEN